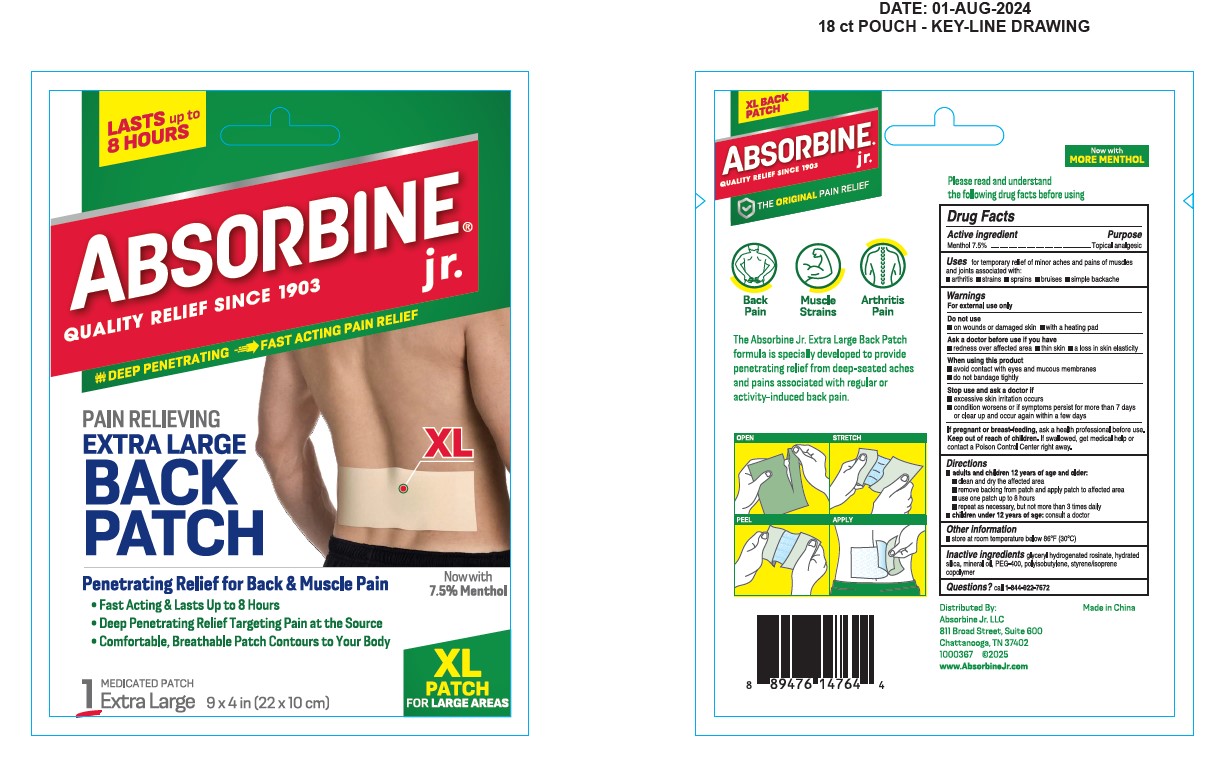 DRUG LABEL: Absorbine Jr Back Patch
NDC: 69693-421 | Form: PATCH
Manufacturer: Clarion Brands LLC.
Category: otc | Type: HUMAN OTC DRUG LABEL
Date: 20251228

ACTIVE INGREDIENTS: MENTHOL 7500 mg/1 h
INACTIVE INGREDIENTS: HYDRATED SILICA; MPEG-400-GLY-NEU-GALNAC-THR; GLYCERYL ROSINATE; MINERAL OIL; POLYISOBUTYLENE (1000 MW); STYRENE/ISOPRENE COPOLYMER (28:72; 210000 MW)

ACTIVE INGREDIENT

Menthol 7.5%

PURPOSE

Topical Analgesic

INDICATIONS AND USAGE

For temporary relief of minor aches and pains of muscles and joints associated with:

- simple backache
- arthritis
- sprains
- strains
- bruises

WARNINGS

For external use only.

Do not use

- on wounds or damaged skin
- with a heating pad

Ask a doctor before use if you have

- redness over affected area

When using this product

- avoid contact with eyes and mucous membranes
- do not bandage tightly

INDICATIONS AND USAGE

- adults and children 12 years of age and older apply to the affected area no more than 3 to 4 times daily
- open pouch & remove patch
- peel off protective film and apply sticky side to affected area
- children under 12 years of age consult a doctor

INACTIVE INGREDIENT

- glyceryl hydrogenated rosinate
- hydrated silica
- mineral oil
- PEG-400
- polyisobutylene
- styrene/isoprene copolymer

QUESTIONS

call 1-844-922-7672

Keep out of reach of children.

If swallowed, get medical help or contact a Poison Control Center right away.

Stop use and ask a doctor if

- condition worsens or if symptoms persist for more than 7 days or clear up and occur again within a few days
- excessive skin irritation occurs

DOSAGE AND ADMINISTRATION

Menthol 7.5%

PACKAGE LABEL

Lasts up to 8 Hours!
Absorbine jr.®
QUALITY RELIEF SINCE 1903
DEEP PENETRATING & FAST ACTING PAIN RELIEF
Extra Large Back Patch

7.5% Menthol
Deep Penetrating Relief for Back & Muscle Pain
• Fast Acting & Lasts Up to 8 Hours
• Deep Penetrating Relief Targeting Pain at the Source
• Comfortable, Breathable Patch Contours to Your Body
Medicated Patch
1 EXTRA LARGE 9 × 4 in (22× 10 cm)

TARGETED for Shoulders, Neck & Arms

Absorbine jr.®
QUALITY RELIEF SINCE 1903
THE ORIGINAL PAIN RELIEF
• Back Pain

- Muscle Strains
- Arthritis Pain

The Absorbine Jr. Extra Large Back Patch formual is specially developed to provide penetrating relief from deep-seated aches and pains associated with regular or activity-induced back pain.

Distributed by:
Absorbine Jr. LLC
811 Broad Street, Suite 600
Chattanooga, TN 37402
1000367 @2025
www.absorbinejr.com
Made in China